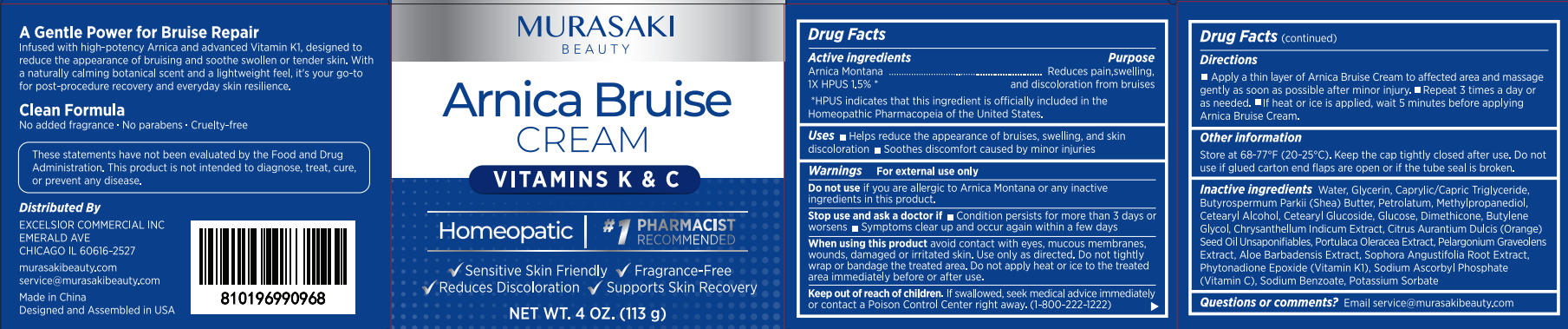 DRUG LABEL: Murasaki Beauty Arnica Bruise Cream
NDC: 87212-001 | Form: CREAM
Manufacturer: Excelsior Commercial Inc
Category: homeopathic | Type: HUMAN OTC DRUG LABEL
Date: 20260228

ACTIVE INGREDIENTS: ARNICA MONTANA 1.695 g/113 g
INACTIVE INGREDIENTS: ALOE BARBADENSIS LEAF JUICE; PHYTONADIONE EPOXIDE; SODIUM ASCORBYL PHOSPHATE; PELARGONIUM GRAVEOLENS WHOLE; WATER; SODIUM BENZOATE; CAPRYLIC/CAPRIC TRIGLYCERIDE; POTASSIUM SORBATE; LEVOGLUCOSE; BUTYLENE GLYCOL; GLYCERIN; PETROLATUM; PORTULACA OLERACEA WHOLE; CETEARYL ALCOHOL; CETEARYL GLUCOSIDE; CITRUS AURANTIUM DULCIS (ORANGE) SEED OIL; BUTYROSPERMUM PARKII (SHEA) BUTTER; SOPHORA FLAVESCENS ROOT; METHYLPROPANEDIOL; DIMETHICONE; CHRYSANTHELLUM INDICUM WHOLE

Update - 87212-001

ACTIVE INGREDIENT

Arnica Montana
1X HPUS 1.5%

PURPOSE

Reduces pain,swelling.and discoloration from bruises

*HPUS indicates that this ingredient is officially included in the Homeopathic Pharmacopeia of the United States.

DOSAGE AND ADMINISTRATION

- Helps reduce the appearance of bruises, swelling, and skin discoloration
- Soothes discomfort caused by minor injuries

WARNINGS

For external use only

DO NOT USE

if you are allergic to Arnica Montana or any inactive ingredients in this product.

ASK DOCTOR

- Condition persists for more than 3 days or worsens
- Symptoms clear up and occur again within a few days

WHEN USING

avoid contact with eyes, mucous membraneswounds, damaged or irritated skin. Use only as directed. Do not tightly wrap or bandage the treated area. Do not apply heat or ice to the treated area immediately before or after use.

KEEP OUT OF REACH OF CHILDREN

lf swallowed, seek medical advice immediately or contact a Poison Control Center right away.(1-800-222-1222)

INDICATIONS AND USAGE

- Apply a thin layer of Arnica Bruise Cream to affected area and massage gently as soon as possible after minor injury.
- Repeat 3 times a day or as needed.
- lf heat or ice is applied, wait 5 minutes before applying Arnica Bruise Cream.

OTHER SAFETY INFORMATION

Store at 68-77°F(20-25°C). Keep the cap tightly closed after use. Do not use if glued carton end flaps are open or if the tube seal is broken.

INACTIVE INGREDIENT

Water, Glycerin, Caprylic/Capric Triglyceride,Butyrospermum Parkii (Shea) Butter, Petrolatum, Methylpropanediol,Cetearyl Alcohol, Cetearyl Glucoside, Glucose, Dimethicone, Butylene Glycol, Chrysanthellum Indicum Extract, Citrus Aurantium Dulcis (Orange) Seed Oil Unsaponifiables, Portulaca Oleracea Extract, Pelargonium Graveolens Extract, Aloe Barbadensis Extract,
Sophora Angustifolia Root Extract, Phytonadione Epoxide (Vitamin Kl), Sodium Ascorbyl Phosphate(Vitamin C), Sodium Benzoate, Potassium Sorbate

QUESTIONS

Email: service@murasakibeauty.com